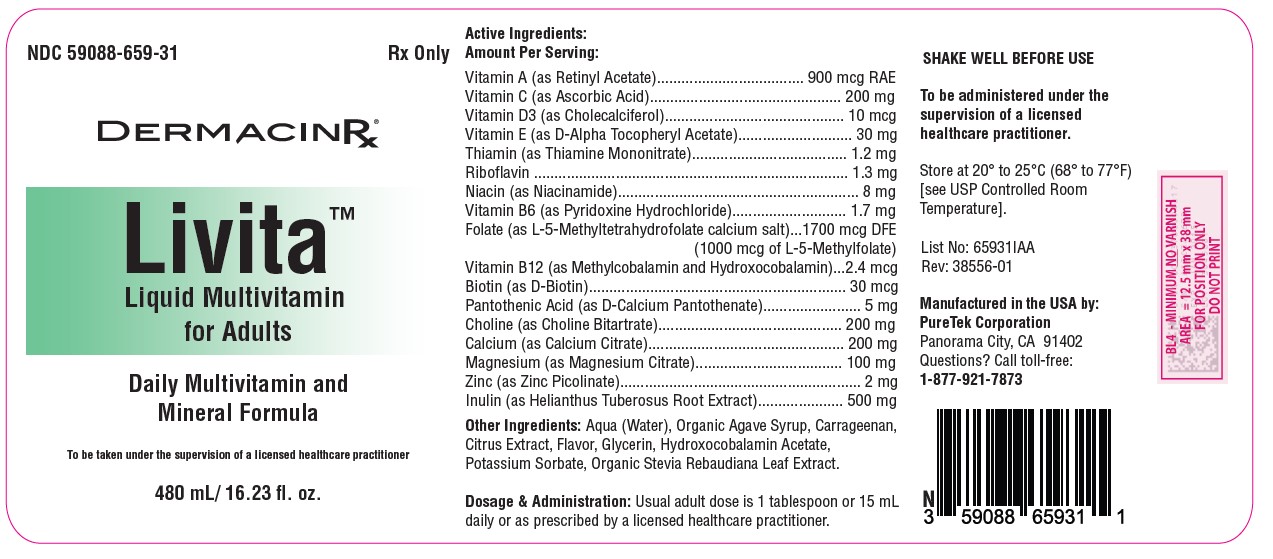 DRUG LABEL: Livita Adults
NDC: 59088-659 | Form: LIQUID
Manufacturer: PureTek Corporation
Category: prescription | Type: HUMAN PRESCRIPTION DRUG LABEL
Date: 20241217

ACTIVE INGREDIENTS: CHOLINE BITARTRATE 200 mg/15 mL; CHOLECALCIFEROL 10 ug/15 mL; VITAMIN A ACETATE 900 ug/15 mL; ASCORBIC ACID 200 mg/15 mL; .ALPHA.-TOCOPHEROL ACETATE, D- 30 mg/15 mL; THIAMINE MONONITRATE 1.2 mg/15 mL; RIBOFLAVIN 1.3 mg/15 mL; NIACINAMIDE 8 mg/15 mL; PYRIDOXINE HYDROCHLORIDE 1.7 mg/15 mL; LEVOMEFOLATE CALCIUM 1000 ug/15 mL; METHYLCOBALAMIN 2.4 ug/15 mL; BIOTIN 30 ug/15 mL; ZINC PICOLINATE 2 mg/15 mL; MAGNESIUM CITRATE 100 mg/15 mL; CALCIUM PANTOTHENATE 5 mg/15 mL; CALCIUM CITRATE 200 mg/15 mL; INULIN 500 mg/15 mL
INACTIVE INGREDIENTS: AGAVE TEQUILANA JUICE; POTASSIUM SORBATE; CARRAGEENAN; WATER; GLYCERIN; STEVIA REBAUDIUNA LEAF; CITRUS FRUIT

Livita Adult
Liquid Multivitamin

DESCRIPTION:

Active Ingredients:
Amount Per Serving:

Vitamin A (as Retinyl Acetate).................................... 900 mcg RAE
Vitamin C (as Ascorbic Acid)............................................... 200 mg
Vitamin D3 (as Cholecalciferol)............................................ 10 mcg
Vitamin E (as D-Alpha Tocopheryl Acetate)............................ 30 mg
Thiamin (as Thiamine Mononitrate)...................................... 1.2 mg
Riboflavin ............................................................................. 1.3 mg
Niacin (as Niacinamide)........................................................... 8 mg
Vitamin B6 (as Pyridoxine Hydrochloride)............................ 1.7 mg
Folate (as L-5-Methyltetrahydrofolate calcium salt)...1700 mcg DFE
(1000 mcg of L-5-Methylfolate)
Vitamin B12 (as Methylcobalamin and Hydroxocobalamin)...2.4 mcg
Biotin (as D-Biotin)............................................................... 30 mcg
Pantothenic Acid (as D-Calcium Pantothenate)........................ 5 mg
Choline (as Choline Bitartrate)............................................. 200 mg
Calcium (as Calcium Citrate)................................................ 200 mg
Magnesium (as Magnesium Citrate).................................... 100 mg
Zinc (as Zinc Picolinate)........................................................... 2 mg
Inulin (as Helianthus Tuberosus Root Extract)..................... 500 mg

Other Ingredients: Aqua (Water), Organic Agave Syrup, Carrageenan, Citrus Extract, Flavor, Glycerin, Hydroxocobalamin Acetate, Potassium Sorbate, Organic Stevia Rebaudiana Leaf Extract.

INDICATIONS AND USAGE:

Livita™ liquid is indicated to provide significant amounts of essential vitamins and minerals, including Vitamins A, C, D, E, thiamine, riboflavin, niacin, vitamin B6, vitamin B12, folate, calcium, magnesium, and zinc, to supplement the diet. This comprehensive nutrient profile helps prevent nutritional deficiencies of these vitamins and minerals, ensuring that the specific dietary needs of adults and children are met to support overall health, energy, and vitality. The product is specially formulated to target common vitamin and mineral gaps in adults, thus promoting optimal health, immune function, bone strength, and metabolic balance. It is intended to be used under the guidance of a licensed healthcare practitioner to ensure that any potential for nutritional deficiency is addressed in a manner that supports the individual's overall health and wellbeing.

Contraindications:

This product is contraindicated in patients with known hypersensitivity to any of its ingredients.

WARNING:

In case of accidental overdose, seek professional assistance or contact a Poison Control Center immediately.

Precaution Section

Folate doses above 0.1 mg daily may obscure pernicious anemia, in that hematologic remission can occur while neurological manifestations remain progressive. There is a potential danger in administering folate to patients with undiagnosed anemia since folate may obscure the diagnosis of pernicious anemia by alleviating the hematologic manifestations of the disease while allowing the neurologic complications to progress. This may result in severe nervous system damage before the correct diagnosis is made. Adequate doses of vitamin B12 may prevent, halt, or improve the neurologic changes caused by pernicious anemia.

The patient’s medical conditions and consumption of other drugs, herbs, and/or supplements should be considered.

For use on the order of a licensed healthcare practitioner. Call your doctor about side effects. To report side effects, call PureTek Corporation at 1-877-921-7873 or FDA at 1-800-FDA-1088 or www.fda.gov/medwatch.

Adverse Reactions:

Folate: Allergic sensitizations have been reported following both oral and parenteral administration of folate. Adverse reactions have been reported with specific vitamins and minerals but generally at levels substantially higher than those contained herein. However, allergic, and idiosyncratic reactions are possible at lower levels.

Dosage and Administration:

Livita™ Liquid Multivitamin for Adults: The usual adult dose is 1 tablespoon (15 mL) daily.

How Supplied:

Livita™ Liquid Multivitamin for Adults is available in a 16 fl.oz. bottle with an NDC of 59088-659-31.

All prescription substitutions using this product shall be pursuant to state statutes as applicable. This is not an Orange Book product.

STORAGE:

Do not use if bottle seal is broken.
KEEP THIS AND ALL MEDICATIONS OUT OF THE REACH OF CHILDREN.
Store at controlled room temperature 20° to 25°C (68° to 77°F). [See USP].
Protect from light and moisture and avoid excessive heat.

Livita™

Manufactured in the USA by:
PureTek Corporation
Panorama City, CA 91402
Questions? Call toll-free:
1-877-921-7873